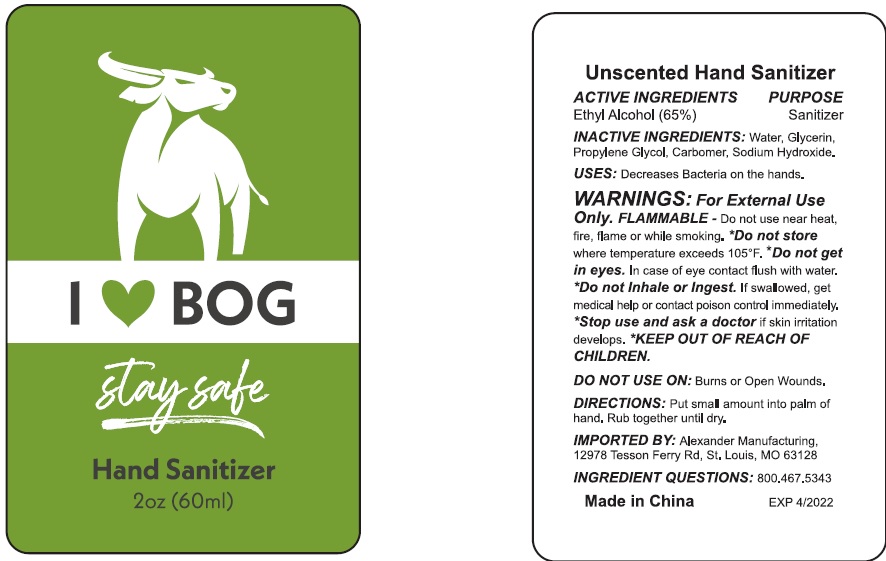 DRUG LABEL: Stay Safe HAND SANITIZER
NDC: 74274-011 | Form: SOLUTION
Manufacturer: Huizhou Bliss Commodity Co., Ltd
Category: otc | Type: HUMAN OTC DRUG LABEL
Date: 20200609

ACTIVE INGREDIENTS: ALCOHOL 65 mL/100 mL
INACTIVE INGREDIENTS: WATER; CARBOMER INTERPOLYMER TYPE A (ALLYL SUCROSE CROSSLINKED); GLYCERIN; PROPYLENE GLYCOL; SODIUM HYDROXIDE

Active ingredient

Ethyl Alcohol 65%

Purpose

Antiseptic

Use

- Decreases bacteria on the hands

Warnings

- For external use only.
- Flammable. Do not use hear heat, fire or flame while smoking.

Do not store where temperature exceeds 105℉.

Do not get in eyes. In case of eye contact flush with water

Do not inhale or ingest.

Stop use and ask a doctor if skin irritation develops.

Do not use on: Burns or open wounds.

If swallowed, get medical help or contact poison control Center immediately.

If swallowed, get medical help or contact a Poison Control Center right away.

Directions

put small amount into palm of hands. Rub together until dry.

Inactive ingredients

Water, glycerin, propyene glycol, carbomer, sodium hydroxide